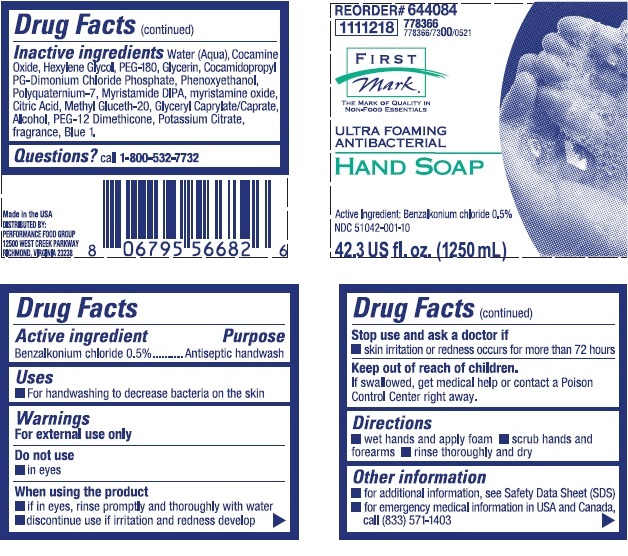 DRUG LABEL: FIRST MARK ULTRA FOAMING ANTIBACTERIAL
NDC: 51042-001 | Form: SOLUTION
Manufacturer: Performance Food Group
Category: otc | Type: HUMAN OTC DRUG LABEL
Date: 20251230

ACTIVE INGREDIENTS: BENZALKONIUM CHLORIDE 5 mg/1 mL
INACTIVE INGREDIENTS: WATER; COCAMINE OXIDE; HEXYLENE GLYCOL; POLYETHYLENE GLYCOL 8000; GLYCERIN; COCAMIDOPROPYL PROPYLENE GLYCOL-DIMONIUM CHLORIDE PHOSPHATE; PHENOXYETHANOL; POLYQUATERNIUM-7 (70/30 ACRYLAMIDE/DADMAC; 1600000 MW); MYRISTIC DIISOPROPANOLAMIDE; MYRISTAMINE OXIDE; ANHYDROUS CITRIC ACID; METHYL GLUCETH-20; GLYCERYL MONO- AND DICAPRYLOCAPRATE; ALCOHOL; PEG-12 DIMETHICONE; POTASSIUM CITRATE; FD&C BLUE NO. 1

Drug Facts

Active Ingredient

Benzalkonium chloride 0.5%

Purpose

Antiseptic handwash

Uses

- For handwashing to decrease bacteria on the skin

Warning

For external use only

Do not use

- in eyes

When using the product

- if in eyes, rinse promptly and thoroughly with water
- discontinue use if irritation and redness develop

Stop use and ask a doctor if

- skin irritation or redness occurs for more than 72 hours

Keep out of reach of children. If swallowed, get medical help or contact a Poison Control Center right away.

Directions

- wet hands and apply foam
- scrub hands and forearms
- rinsethoroughly and dry

Other information

- for additional information, see Safety Data Sheet (SDS)
- for emergency medical information in USA and Canada, call (833) 571-1403

INACTIVE INGREDIENT

Inactive ingredients water (aqua), cocamine oxide, hexylene glycol, PEG-180, glycerin, cocamidopropyl PG-dimonium chloride phosphate, phenoxyethanol, polyquaternium 7, myristamide DIPA, myristamine oxide, citric acid, methyl gluceth-20, glyceryl caprylate/carate, alcohol, PEG-12 dimethicone, potassium citrate, fragrance, blue 1

Questions? call 1-800-532-7732

Principal display panel and representative container

REORDER# 644084

1111218 778366 778366/7300/0521

FIRST MARK

ULTRA FOAMING ANTIBACTERIAL

HAND SOAP

Active Ingredient: Benzalkonium Chloride 0.5%

NDC 51042-001-10

Made in the USA

DISTRIBUTED BY:

PERFORMANCE FOOD GROUP

12500 WEST CREEK PARKWAY

RICHMOND VIRGINIA 23238